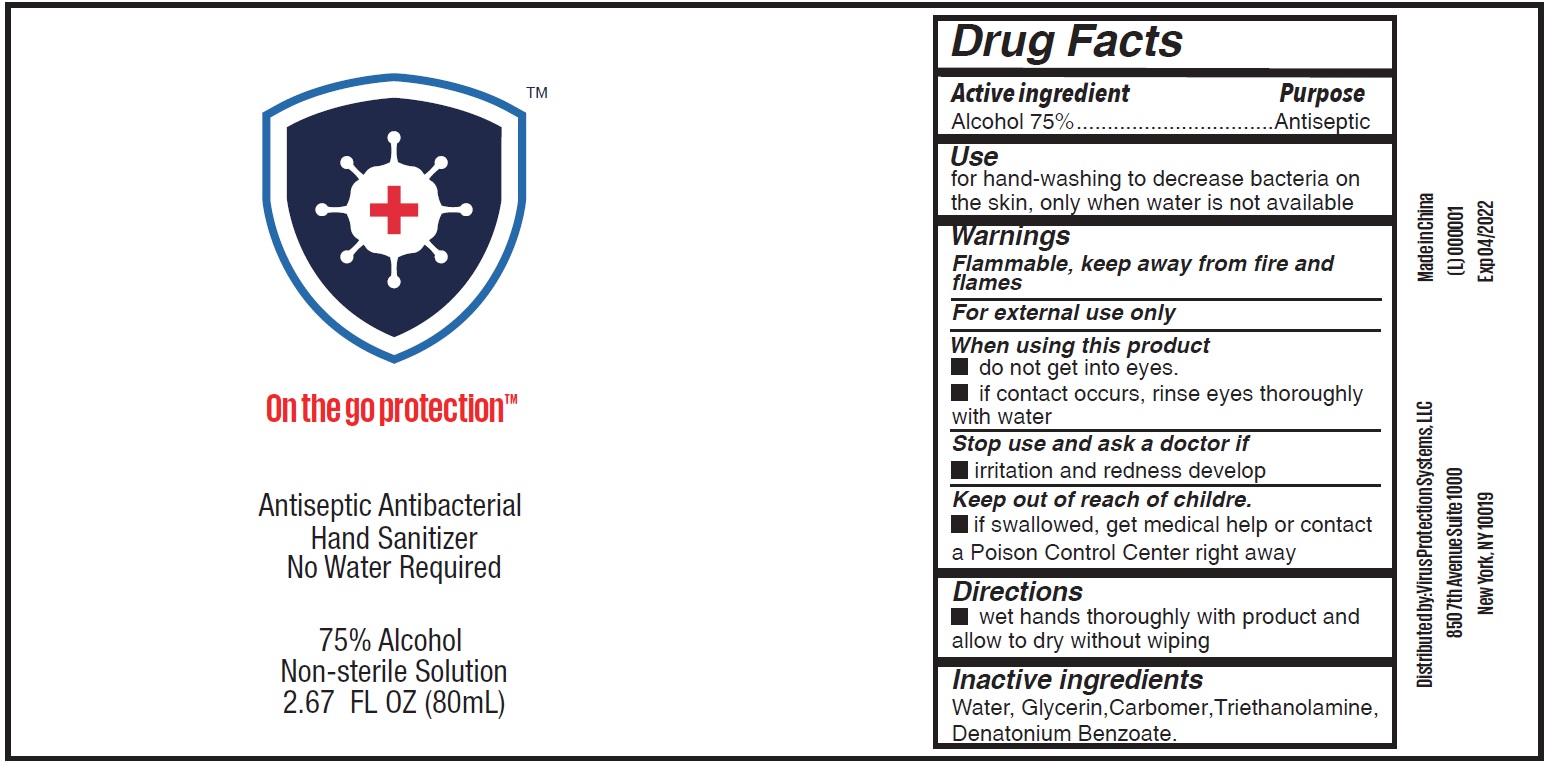 DRUG LABEL: Antiseptic Antibacterial Hand Sanitizer
NDC: 74707-010 | Form: GEL
Manufacturer: Virus Protection Systems,LLC
Category: otc | Type: HUMAN OTC DRUG LABEL
Date: 20231025

ACTIVE INGREDIENTS: ALCOHOL 0.75 mL/1 mL
INACTIVE INGREDIENTS: WATER; GLYCERIN; CARBOMER HOMOPOLYMER, UNSPECIFIED TYPE; TROLAMINE; DENATONIUM BENZOATE

Antiseptic Antibacterial Hand Sanitizer

Active ingredient

Alcohol 75%

Purpose

Antiseptic

Use

for hand-washing to decrease bacteria on the skin, only when water is not available

Warnings

Flammable, keep away from fire or flames

For external use only

When using this product

- do not get into eyes.
- if contact occurs, rinse eyes thoroughly with water

Stop use and ask a doctor if

irritation and redness develop

Keep out of reach of children.

If swallowed get medical help or contact a Poison Control Center right away.

Directions

- wet hands thoroughly with product and allow to dry without wiping

Inactive ingredients

Water, Glycerin, Fragrance, Carbomer, Triethanolamine, Denatonium Benzoate.